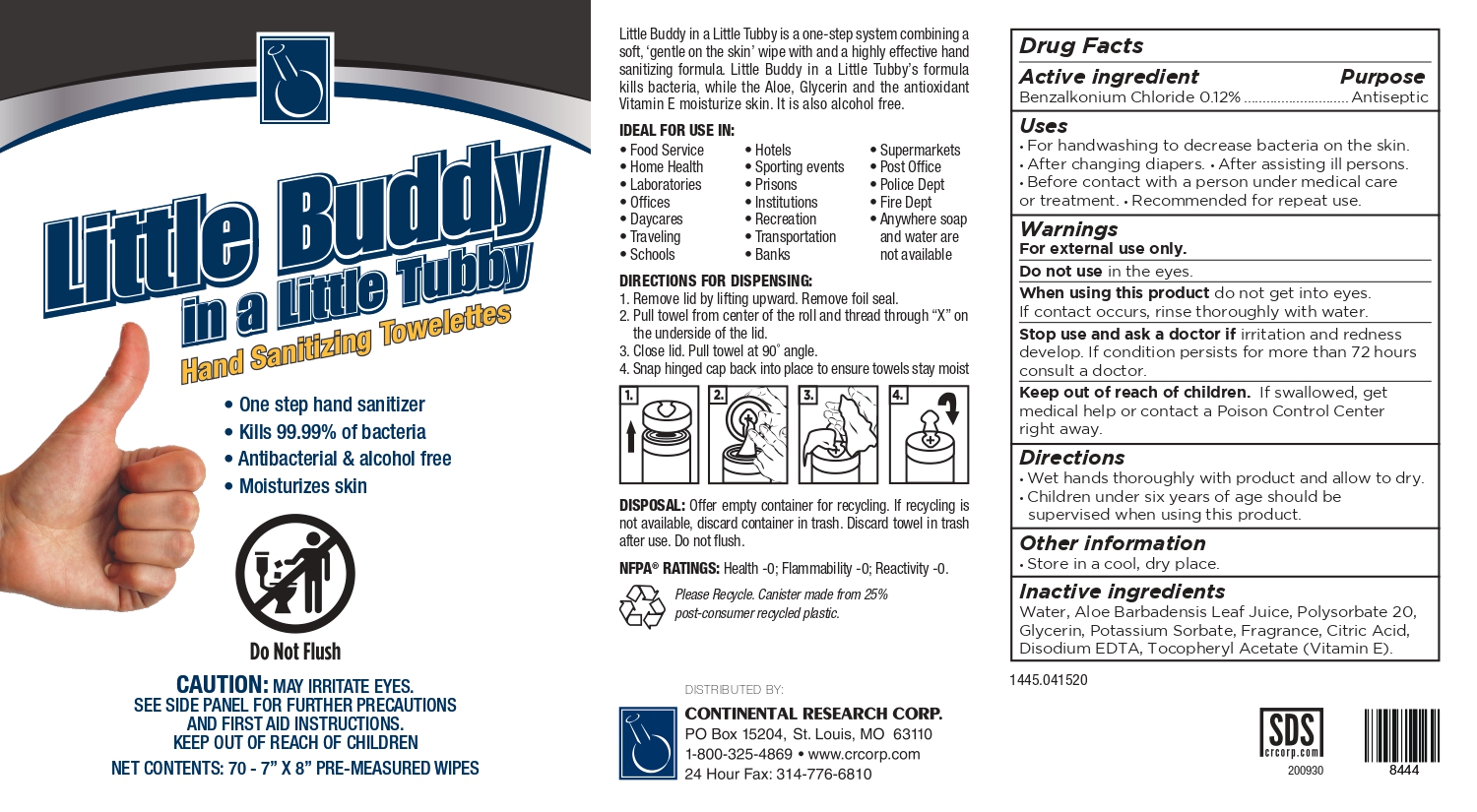 DRUG LABEL: Little Buddy in a Little Tubby
NDC: 64321-123 | Form: CLOTH
Manufacturer: Continental Research Corp
Category: otc | Type: HUMAN OTC DRUG LABEL
Date: 20250123

ACTIVE INGREDIENTS: BENZALKONIUM CHLORIDE 0.12 mg/100 mL
INACTIVE INGREDIENTS: GLYCERIN; POTASSIUM SORBATE; .ALPHA.-TOCOPHEROL ACETATE, D-; POLYSORBATE 20; ANHYDROUS CITRIC ACID; ALOE VERA LEAF; WATER; EDETATE DISODIUM ANHYDROUS

Research Corp-Athea Lab BZK wipes 70

Active Ingredient(s)

Benzalkonium chloride 0.12%

Purpose

Antiseptic

Use

For handwashing to decrease bacteria on the skin. • After changing diapers. • After assisting ill persons. • Before contact with a person under medical care or treatment. • Recommended for repeat use.

Warnings

For external use only.

Do not use in the eyes.

When using this product do not get into eyes. If contact occurs, rinse thoroughly with water.

Stop use and ask a doctor if irritation and redness develop. If condition persists for more than 72 hours consult a doctor.

Keep out of reach of children. If swallowed, get medical help or contact a Poison Control Center right away.

Directions

Wet hands thoroughly with product and allow to dry. • Children under six years of age should be

supervised when using this product.

Other information

Store in a cool, dry place.

Inactive ingredients

Water, Aloe Barbadensis Leaf Juice, Polysorbate 20, Glycerin, Potassium Sorbate, Fragrance, Citric Acid, Disodium EDTA, Tocopheryl Acetate (Vitamin E).

Package Label - Principal Display Panel

70 PCS NDC:64321-123-70